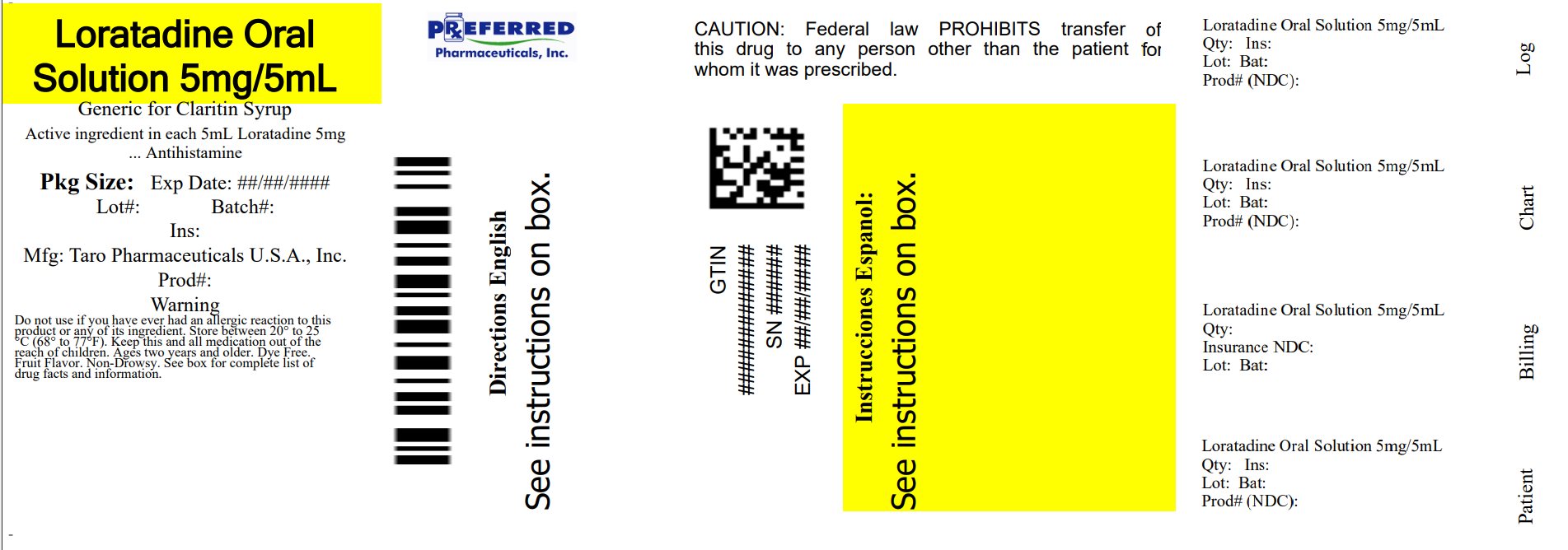 DRUG LABEL: Childrens Loratadine
NDC: 68788-8286 | Form: SOLUTION
Manufacturer: Preferred Pharmaceuticals Inc.
Category: otc | Type: HUMAN OTC DRUG LABEL
Date: 20260115

ACTIVE INGREDIENTS: Loratadine 5 mg/5 mL
INACTIVE INGREDIENTS: BUTYLATED HYDROXYANISOLE; GLYCERIN; SORBITOL; POLYETHYLENE GLYCOL, UNSPECIFIED; PHOSPHORIC ACID; PROPYLENE GLYCOL; WATER; SODIUM BENZOATE; SODIUM PHOSPHATE, MONOBASIC, DIHYDRATE

Childrens Loratadine Oral Solution
Sugar Free

Drug Facts

Active ingredient (in each 5 mL teaspoonful)

Loratadine 5 mg

Purpose

Antihistamine

Uses

temporarily relieves these symptoms due to hay fever or other upper respiratory allergies:

- runny nose
- itchy, watery eyes
- sneezing
- itching of the nose or throat

Warnings

Do not use if you have ever had an allergic reaction to this product or any of its ingredients.

Ask a doctor before use if you have liver or kidney disease. Your doctor should determine if you need a different dose.

When using this product do not take more than directed. Taking more than directed may cause drowsiness.

Stop use and ask a doctor if an allergic reaction to this product occurs. Seek medical help right away.

PREGNANCY OR BREAST FEEDING

If pregnant or breast-feeding, ask a health professional before use.

Keep out of reach of children. In case of overdose, get medical help or contact a Poison Control Center right away. (1-800-222-1222)

Directions

- use only with enclosed dosing cup

adults and children 6 years and over | 2 teaspoonfuls (tsp) daily; do not take more than 2 teaspoonfuls (tsp) in 24 hours
children 2 to under 6 years of age | 1 teaspoonful (tsp) daily; do not take more than 1 teaspoonful (tsp) in 24 hours
children under 2 years of age | ask a doctor
consumers with liver or kidney disease | ask a doctor

Other information

- do not use if bottle wrap imprinted with "SEALED FOR SAFETY" is broken or missing.
- see bottom panel for lot number and expiration date
- store between 20° and 25°C (68° and 77°F)

Inactive ingredients

butylated hydroxyanisole, glycerin, grape flavor, maltitol solution, masking agent, phosphoric acid, polyethylene glycol, propylene glycol, purified water, sodium benzoate, sodium phosphate monobasic dihydrate, sorbitol solution, sucralose powder.

Questions?

Call 1-866-923-4914

Distributed by:
Taro Pharmaceuticals U.S.A., Inc.
Hawthorne, NY 10532

Relabeled By: Preferred Pharmaceuticals Inc.

PRINCIPAL DISPLAY PANEL - 120 mL Bottle Carton

NDC 68788-8286-1

Compare to the
active ingredient
in Children's Claritin®*

Original
Prescription Strength

Children's

Loratadine
Oral Solution
USP, 5 mg/5 mL

(Antihistamine) ALLERGY

Non-Drowsy†

Indoor & Outdoor Allergies

SUGAR FREE

24
Hour

Relief of:

- Sneezing
- Runny Nose
- Itchy, Watery Eyes
- Itchy Throat or Nose

Ages 2 years and older

Dosing Cup
Enclosed

Grape
Flavor

†When taken as directed.
See Drug Facts Panel.

4 FL OZ
(120 mL)